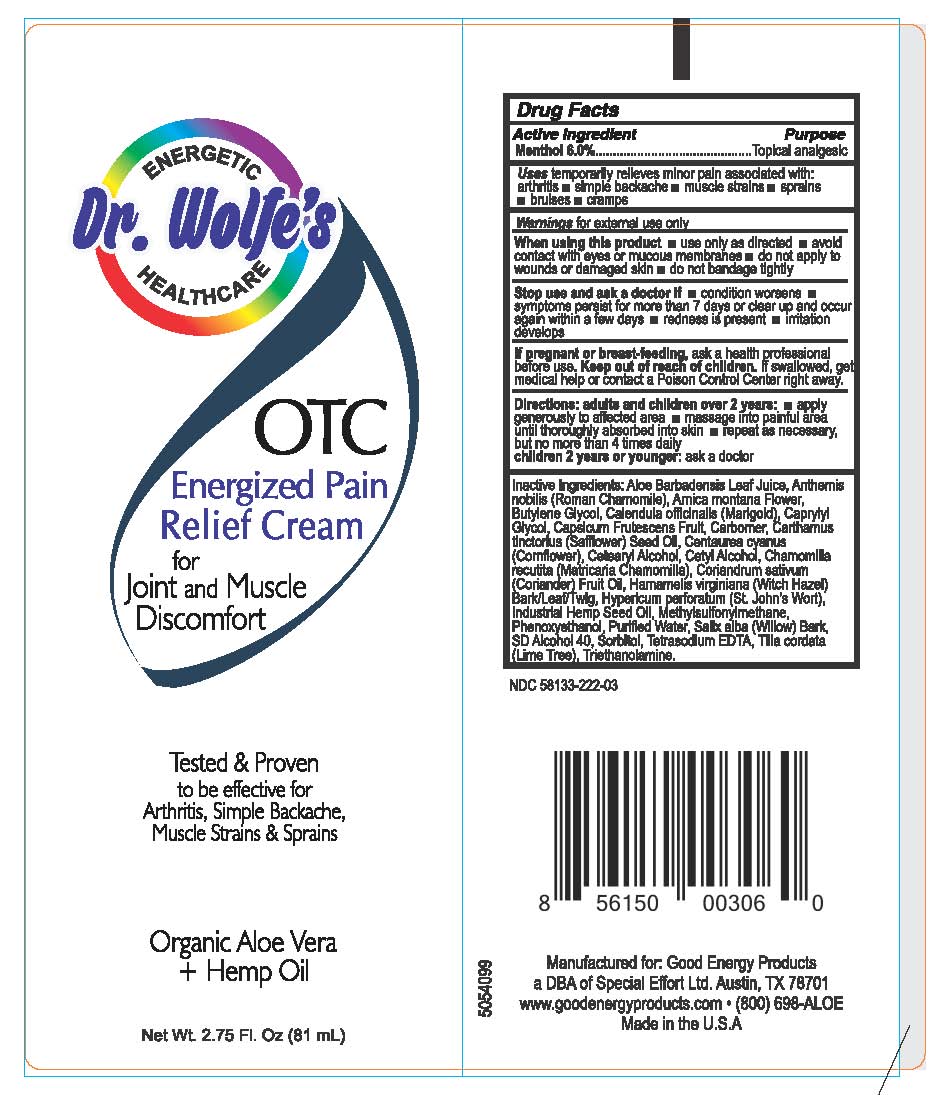 DRUG LABEL: Pain Relief Cream
NDC: 58133-222 | Form: CREAM
Manufacturer: Cosmetic Specialty labs, Inc.
Category: otc | Type: HUMAN OTC DRUG LABEL
Date: 20181031

ACTIVE INGREDIENTS: MENTHOL 6 g/100 mL
INACTIVE INGREDIENTS: ALOE VERA LEAF; TRIETHANOLAMINE LAURYLAMINOPROPIONATE; MATRICARIA CHAMOMILLA; CHAMAEMELUM NOBILE FLOWER; ARNICA MONTANA FLOWER; CALENDULA OFFICINALIS FLOWER; CAPRYLYL GLYCOL; CAPSICUM; CARBOMER HOMOPOLYMER TYPE B (ALLYL SUCROSE CROSSLINKED); CENTAUREA CYANUS FLOWER; CETOSTEARYL ALCOHOL; CETYL ALCOHOL; CORIANDER OIL; HAMAMELIS VIRGINIANA TOP; PHENOXYETHANOL; WATER; SALIX ALBA BARK; ISOPROPYL ALCOHOL; SORBITOL; TILIA X EUROPAEA FLOWER; HEMP; BUTYLENE GLYCOL; HYPERICUM PERFORATUM; 3-((3-CHLOROPHENYL)(4-(METHYLSULFONYL)PHENYL)METHYLENE)DIHYDRO-2(3H)-FURANONE, (3Z)-; DITETRACYCLINE TETRASODIUM EDETATE; CARTHAMUS TINCTORIUS FLOWER OIL

Dr. Wolfe's OTC Energized Pain Relief Cream

Drug Facts

Active Ingredient

Menthol 6.0%

Purpose

Topical analgesic

Uses

temporarily relieves minor pain associated with:

- arthritis
- simple backache
- muscle strains
- sprains
- bruises
- cramps

Warnings

for external use only

When using this product

- use only as directed
- do not bandage tightly
- avoid contact with eyes or mucous membranes
- do not apply to wounds or damaged skin

Stop use and ask a doctor if

- condition worsens
- symptoms persist for more than 7 days or clear up and occur again within a few days
- redness is present
- irritation develops

PREGNANCY OR BREAST FEEDING

If pregnant or breast-feeding, ask a health professional before use.

Keep out of reach of children. If swallowed, get medical help or contact a Poison Control Center right away.

Directions

adults and children over 2 years:

- apply generously to affected area
- massage into painful area until thoroughly absorbed into skin
- repeat as necessary, but no more than 4 times daily

children 2 years or younger: ask a doctor

Inactive ingredients

Aloe Barbadensis Leaf Juice, Anthemis nobilis (Roman Chamomile), Arnica montana, Butylene glycol, Calendula officinalis (Marigold), Capryl glycol, Calpsicum grutescens, Carbomer, Cantharius tinctorious (Safflower) Seed Oil, Centaureacyanus (Cornflower), Cetearyl alcohol, Cetyl alcohol, Chamomila recutita (Matricaria Chamomila), Coriandrum sativum (Coriander), Hamamelis virginiana (Witch Hazel), Bark/Leaf/Twig, Hypericum perforatum (St. John's Wort), Industrial Hemp geed oil, Methylsulfonylmethane, Phenoxyethanol, Purified water,Salix alba (Willow Bark), SD Alcohol40, Sorbitol, Tetrasodium EDTA, Tilla cordata (Lime Tree), Triethanolamine

Manufactured for: Good Energy Products

a DBA of Special Effort Ltd. Austin, TX 78701

www.goodenergyproducts.com (800) 698-ALOE

Made in the U.S.A.